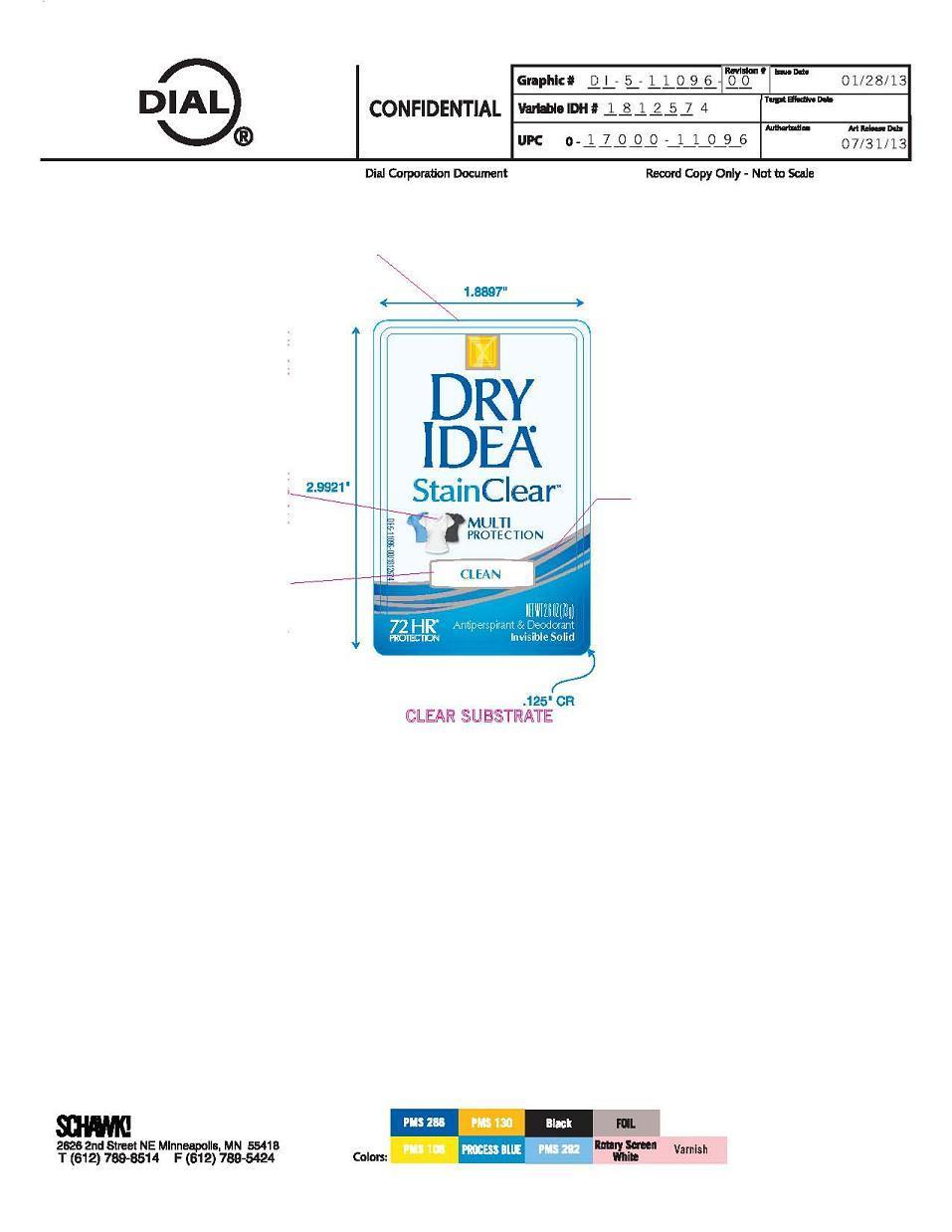 DRUG LABEL: Dry Idea
NDC: 51815-224 | Form: STICK
Manufacturer: VVF Illinois Services
Category: otc | Type: HUMAN OTC DRUG LABEL
Date: 20140402

ACTIVE INGREDIENTS: Aluminum Zirconium Tetrachlorohydrex GLY 13.87 g/73 g
INACTIVE INGREDIENTS: WATER; HIGH DENSITY POLYETHYLENE; DODECAMETHYLPENTASILOXANE; C12-15 ALKYL BENZOATE; PROPYLENE GLYCOL; CETYL PEG/PPG-10/1 DIMETHICONE (HLB 2); PEG/PPG-14/4 DIMETHICONE; SYNTHETIC WAX (1200 MW)

Dry Idea Clean

Active Ingredient

Aluminum Zirconium Tetrachlorohydrex GLY 19.0%

Purpose

Antiperspirant

Warnings

For external use only. do not use on broken skin.

Stop use and ask doctor.

Stop use and ask a doctor if rash or irritation occurs.

Keep out of reach of children

If swallowed, get medical help or contact a poison control center right away.

ask a doctor before use if you have kidney disease.

use

Reduces underarm perspiration Extra effective

Inactive ingredients

water, polyethylene, cyclohexasiloxane, C12-15 alkyl benzoate, propylene glycol, cetyl PEG/PPG-10-1 dimethicone, bis-PEG/PPG-14/14 dimethicone/dimethicone, synthetic wax

Directions

Apply to underarms only.

Questions?

1-800-258-DIAL